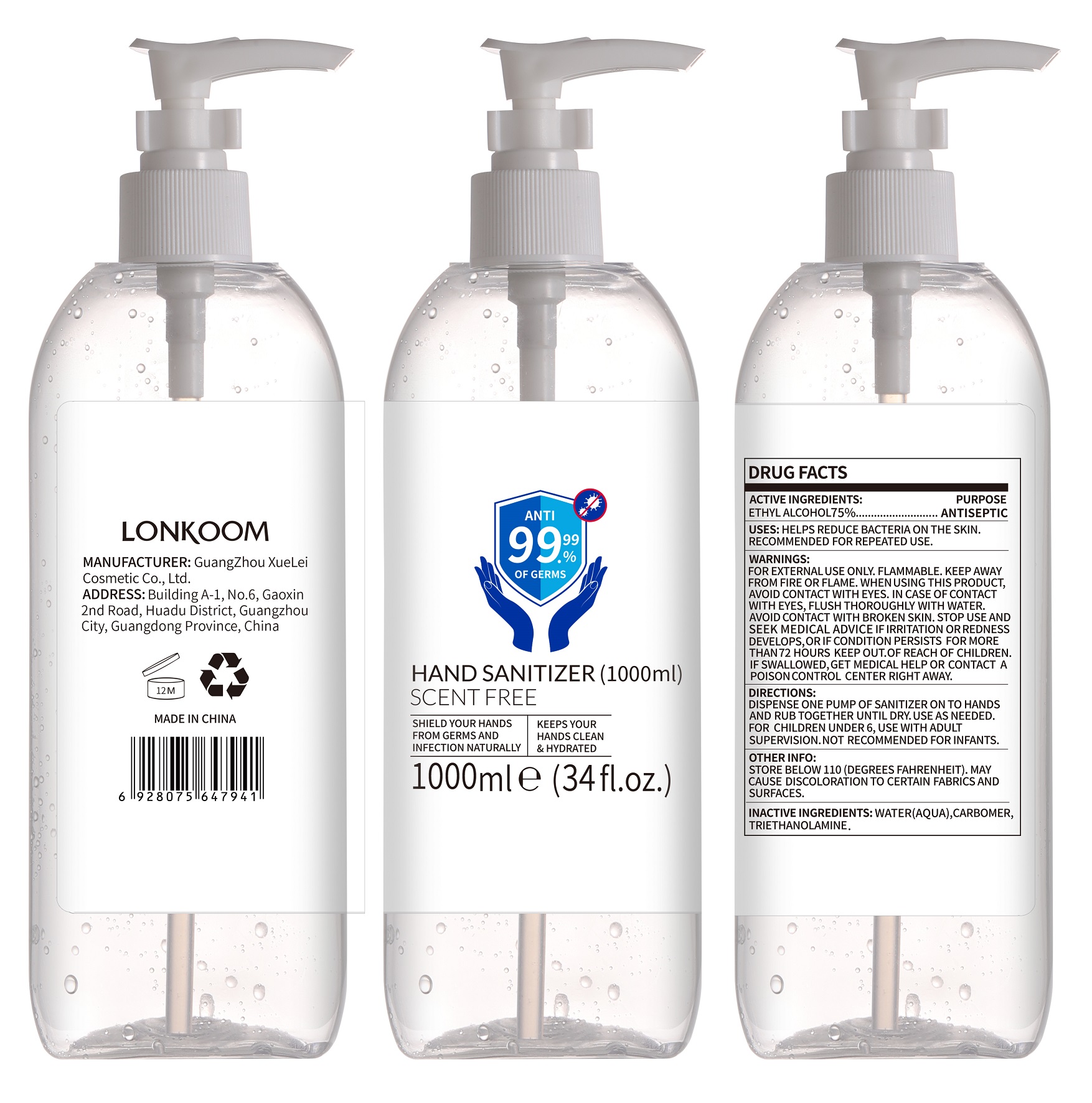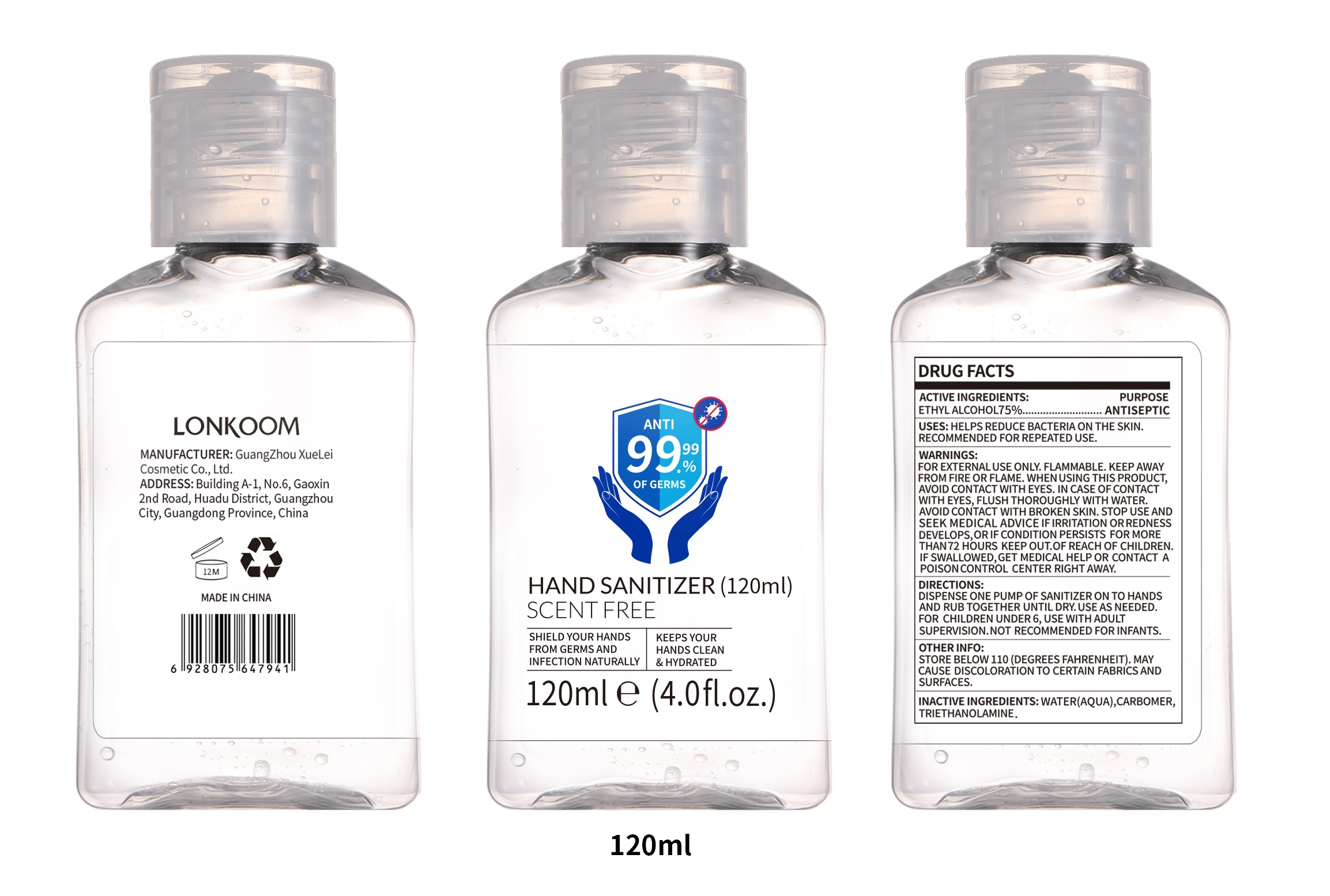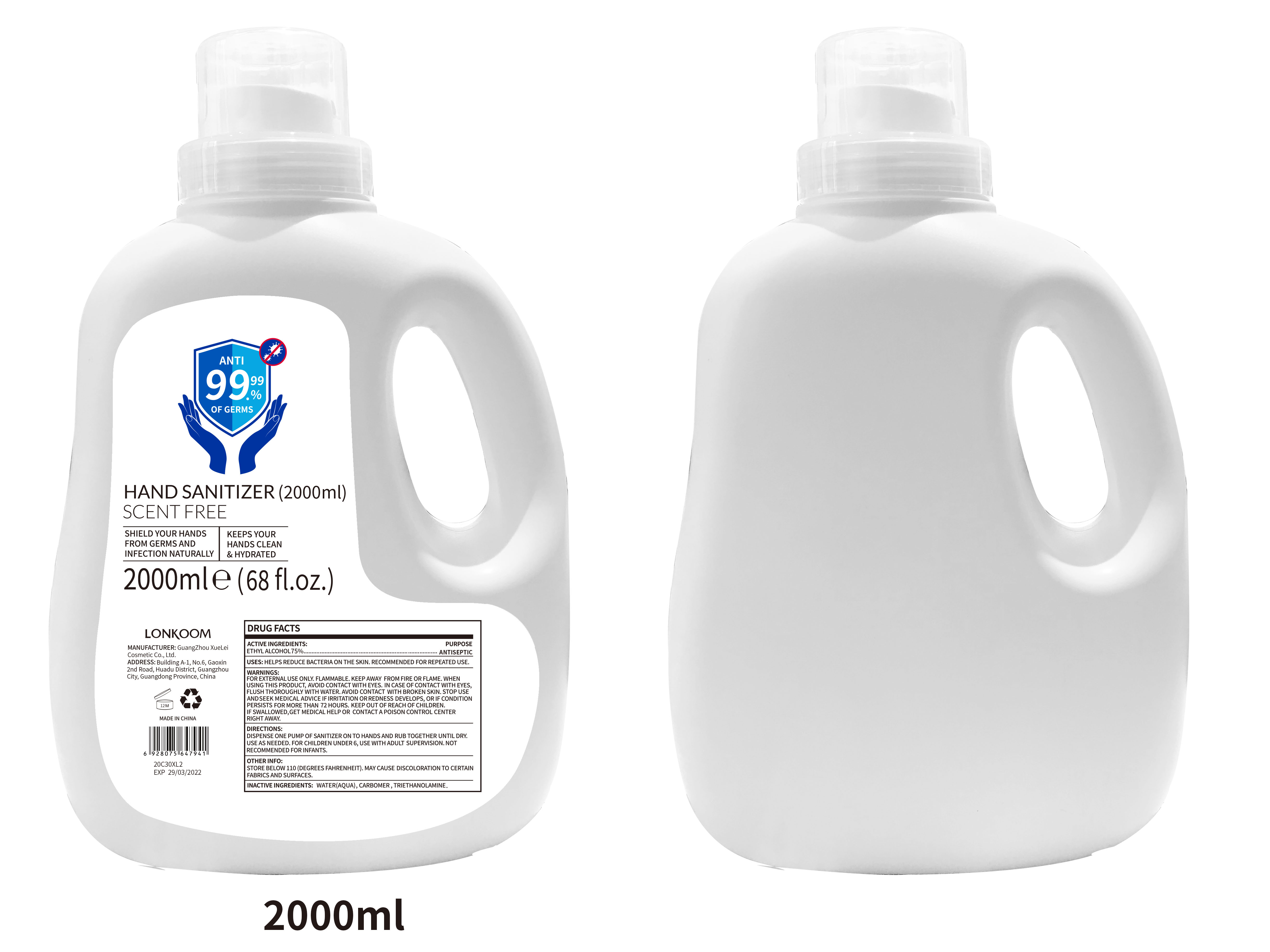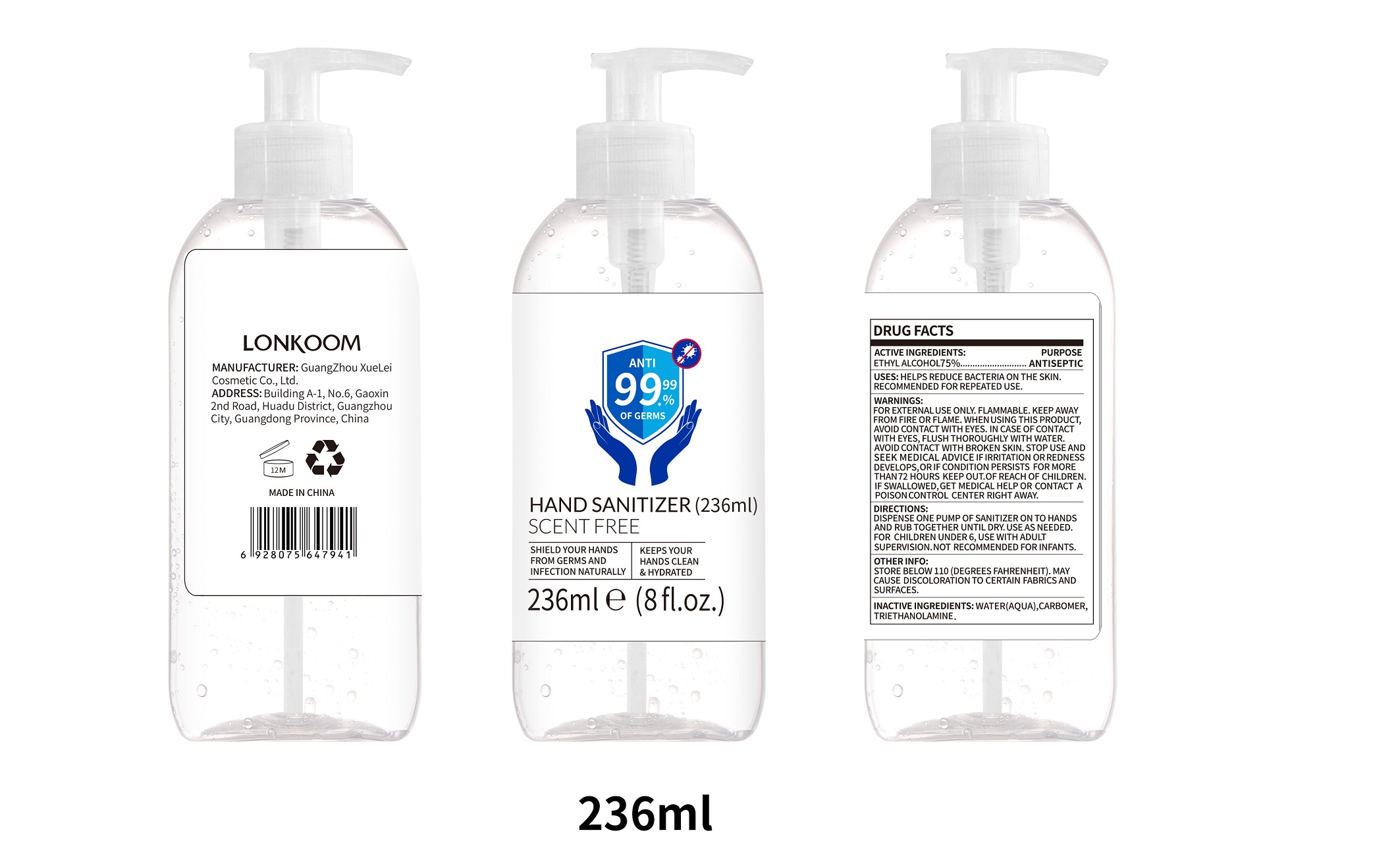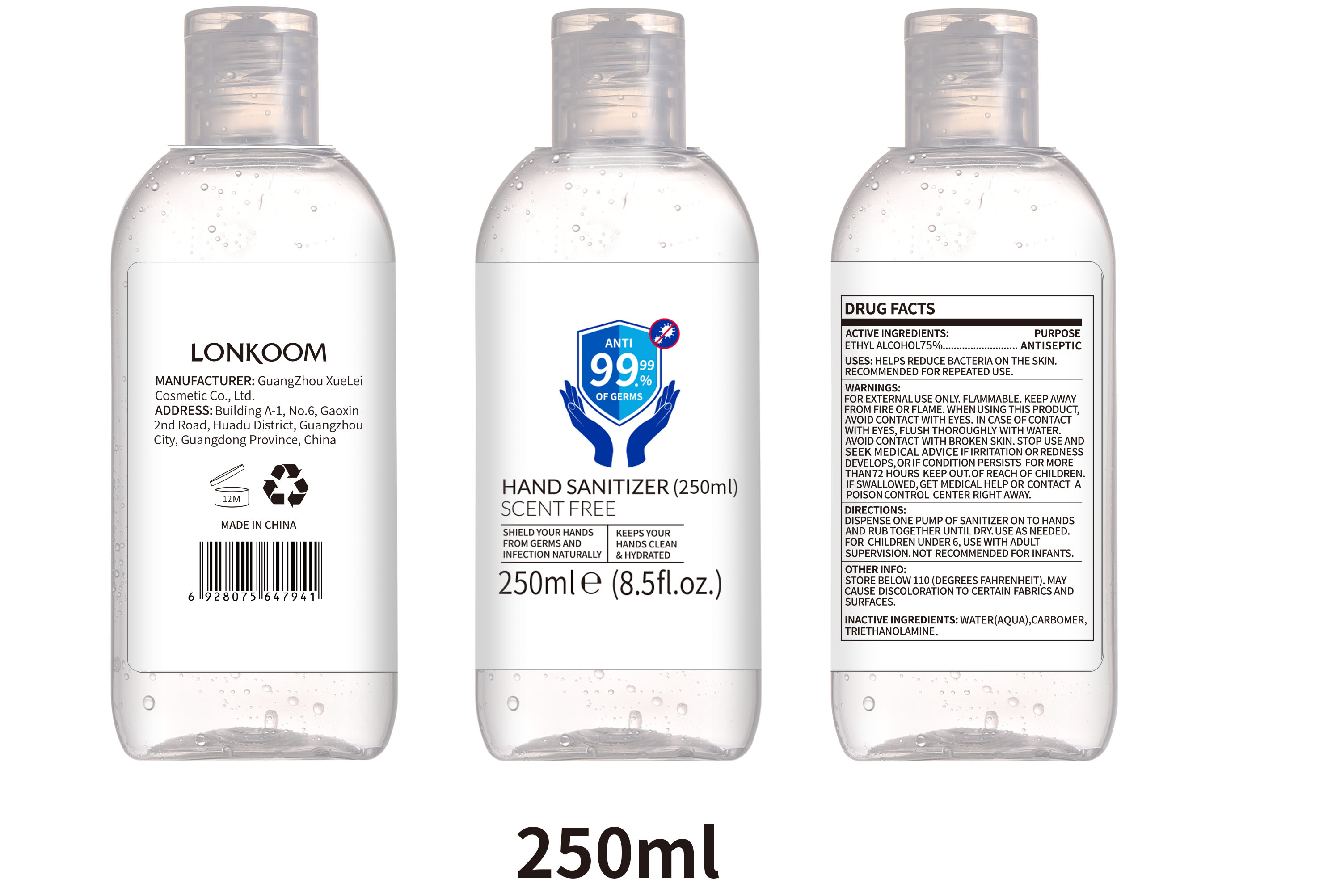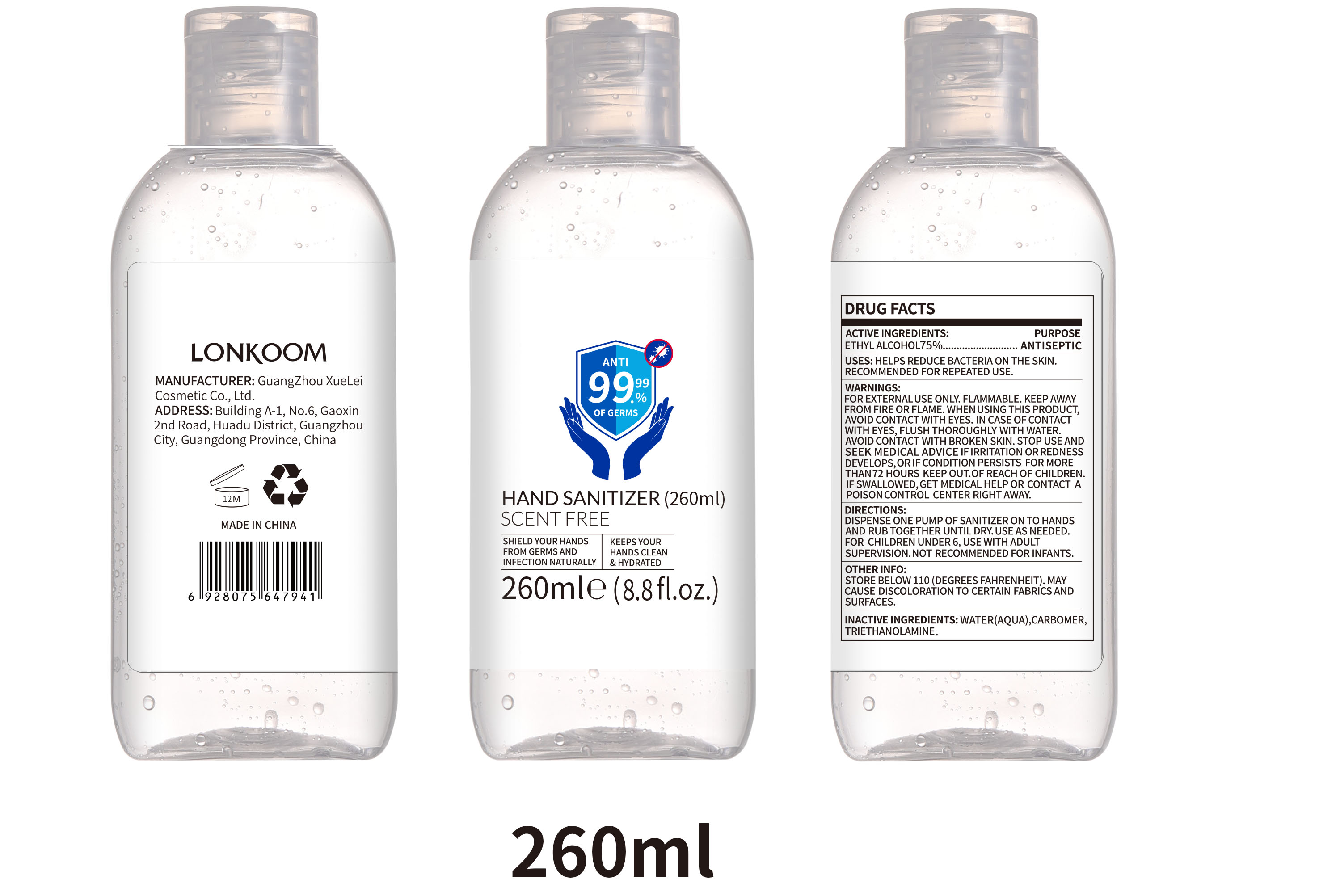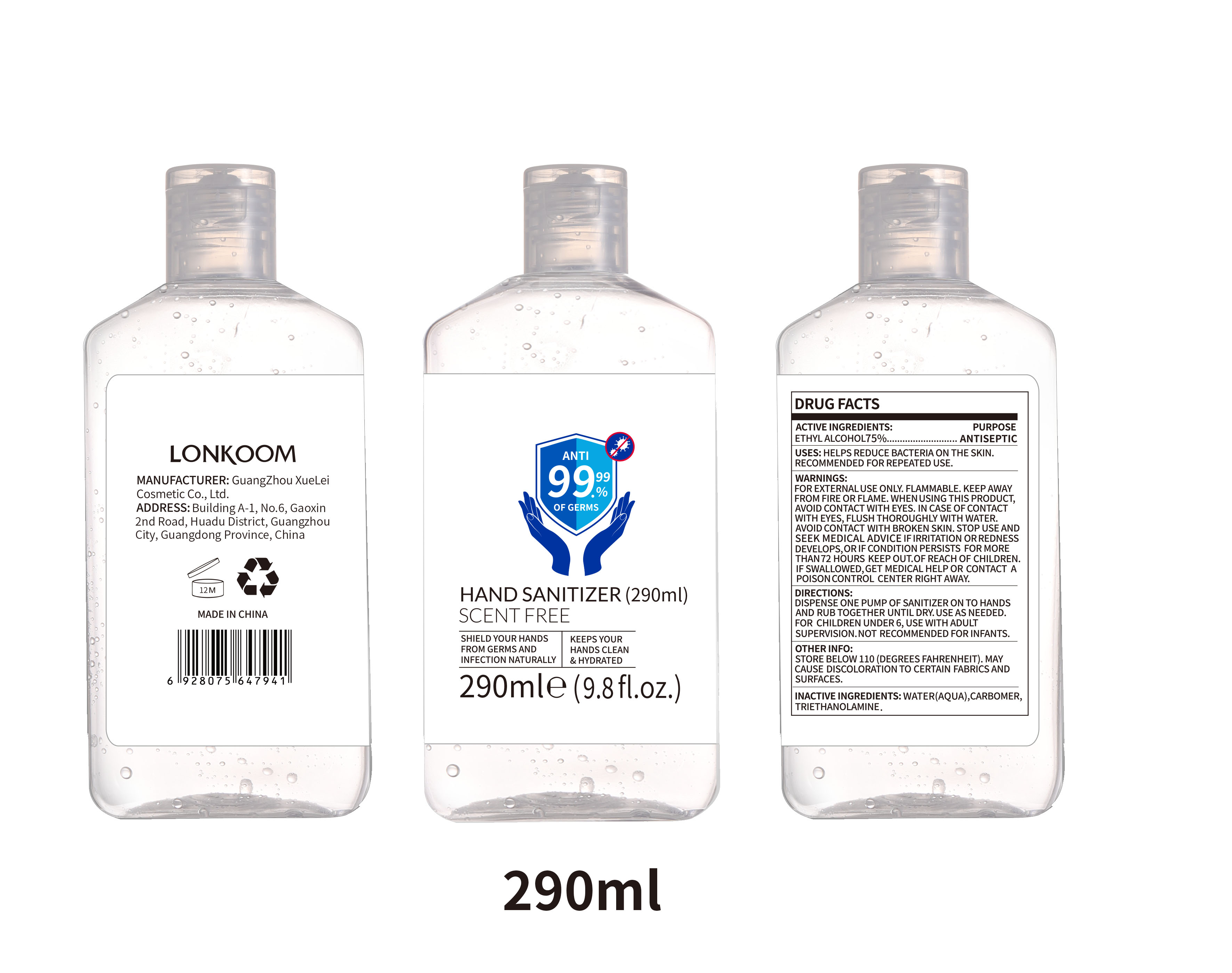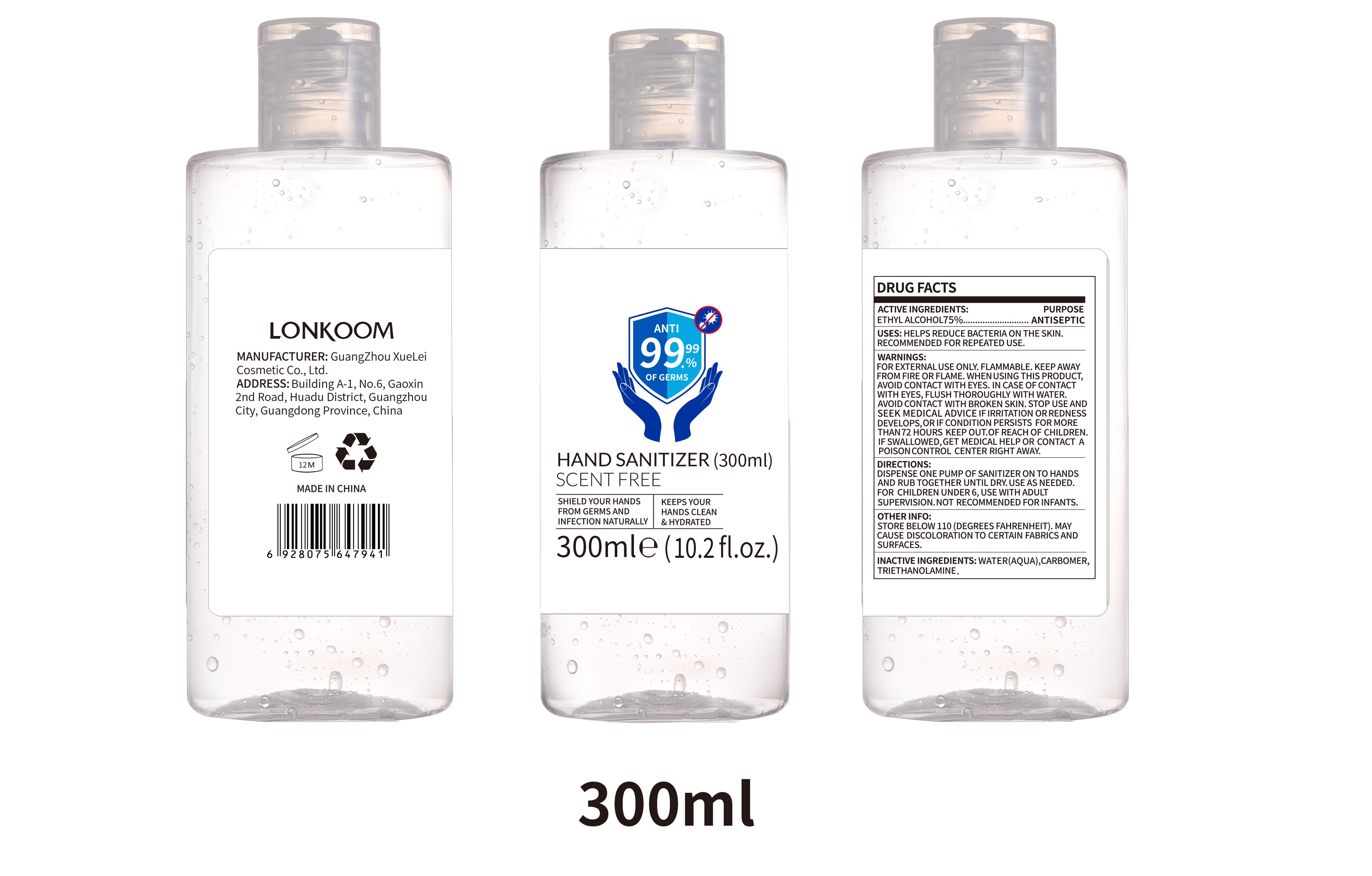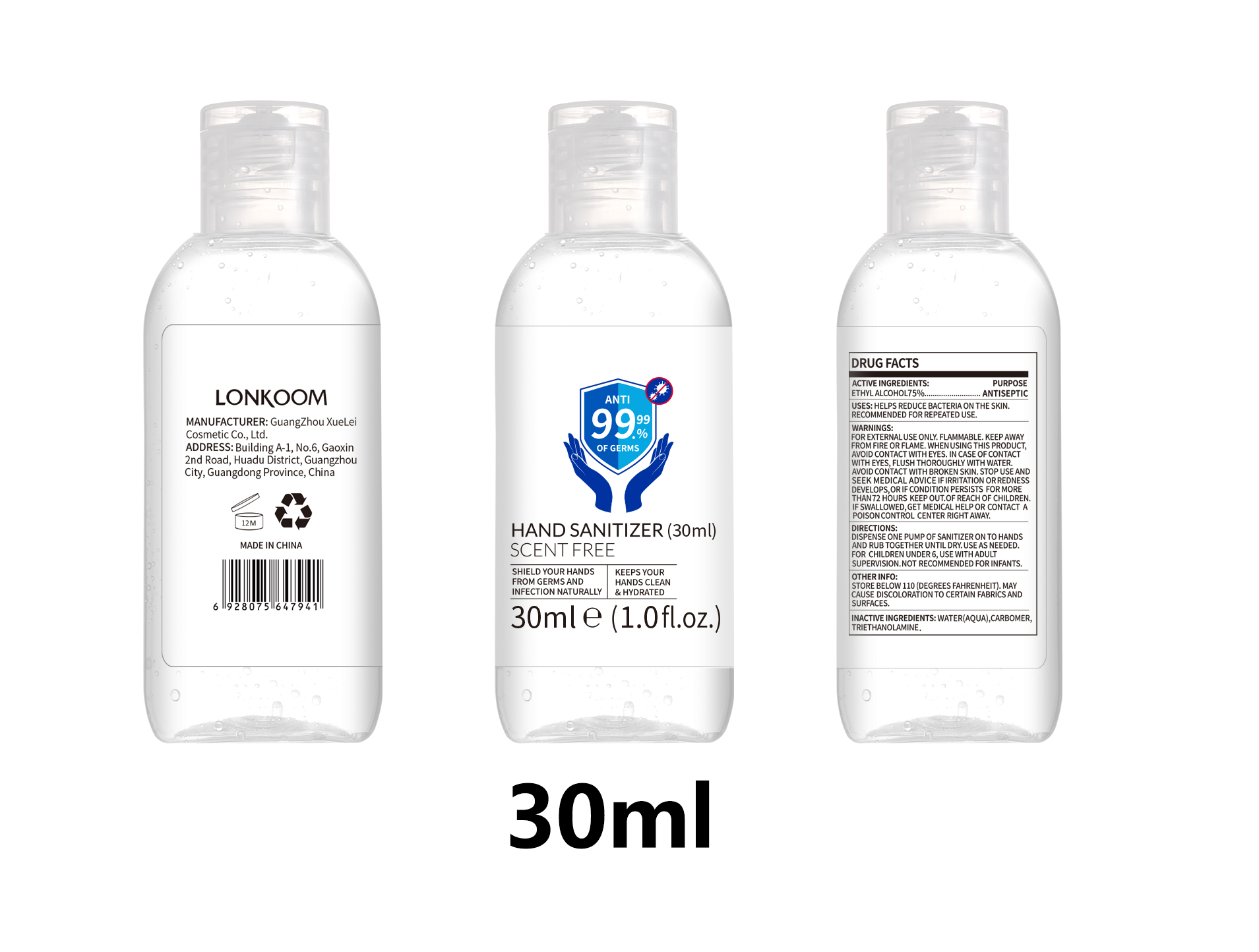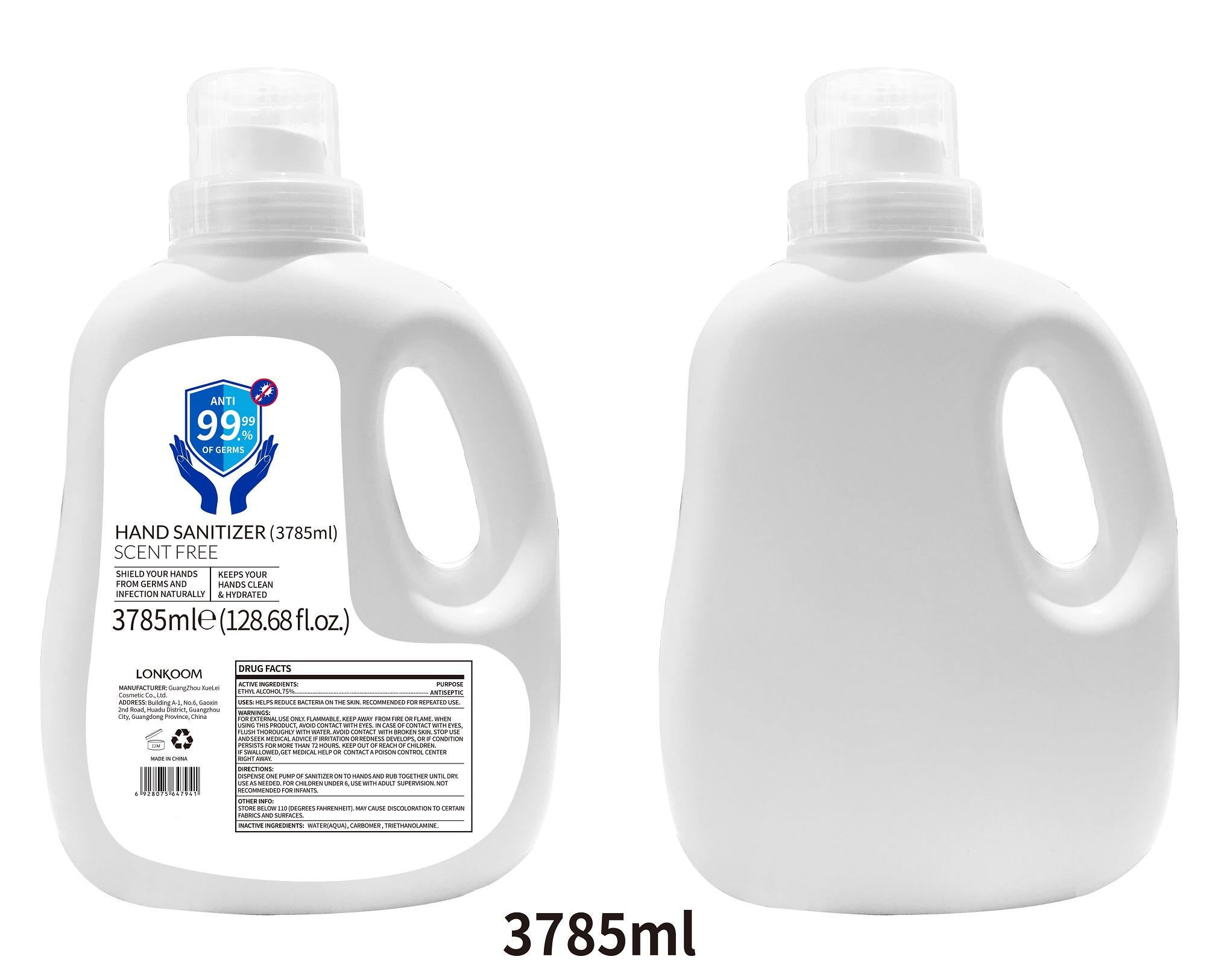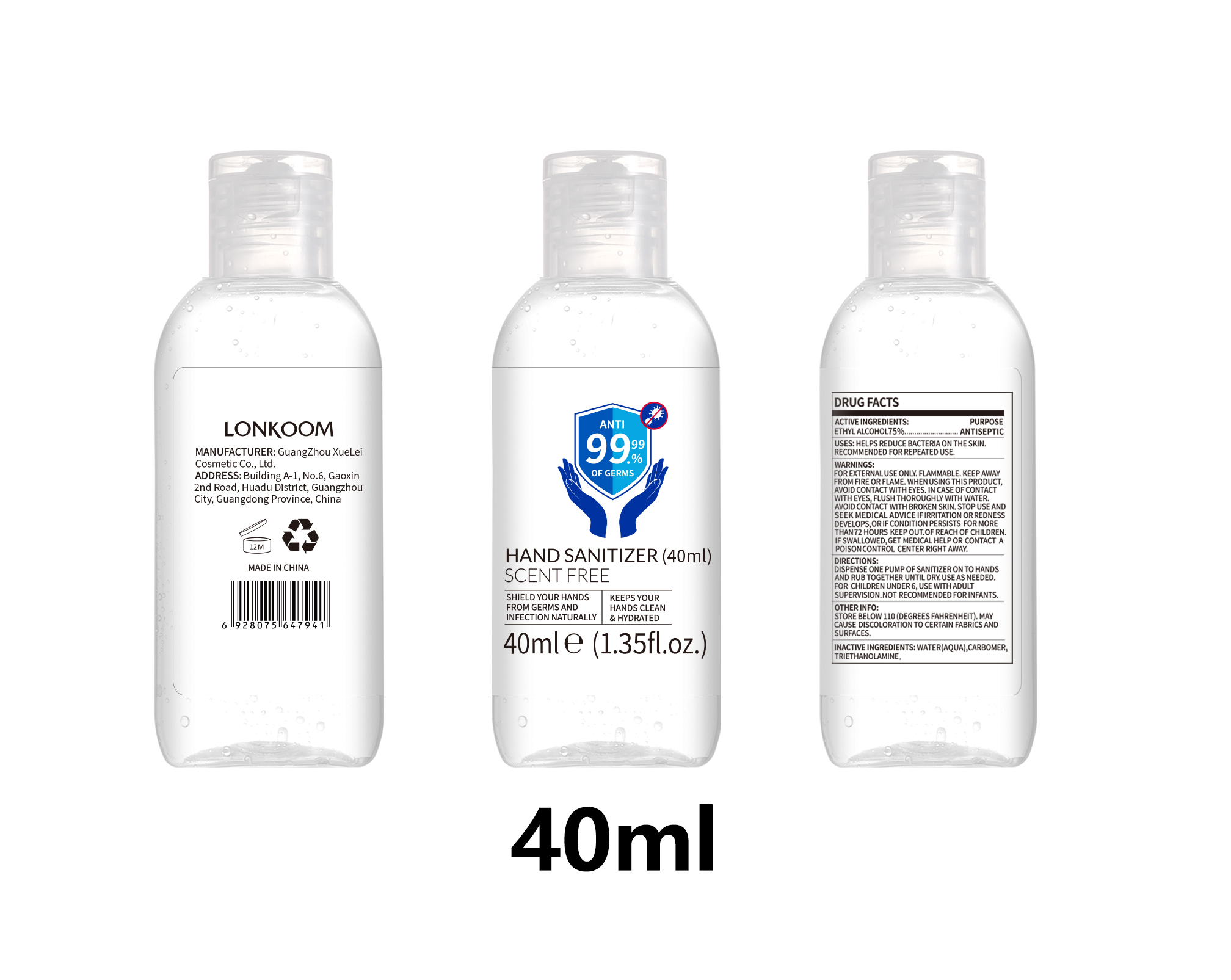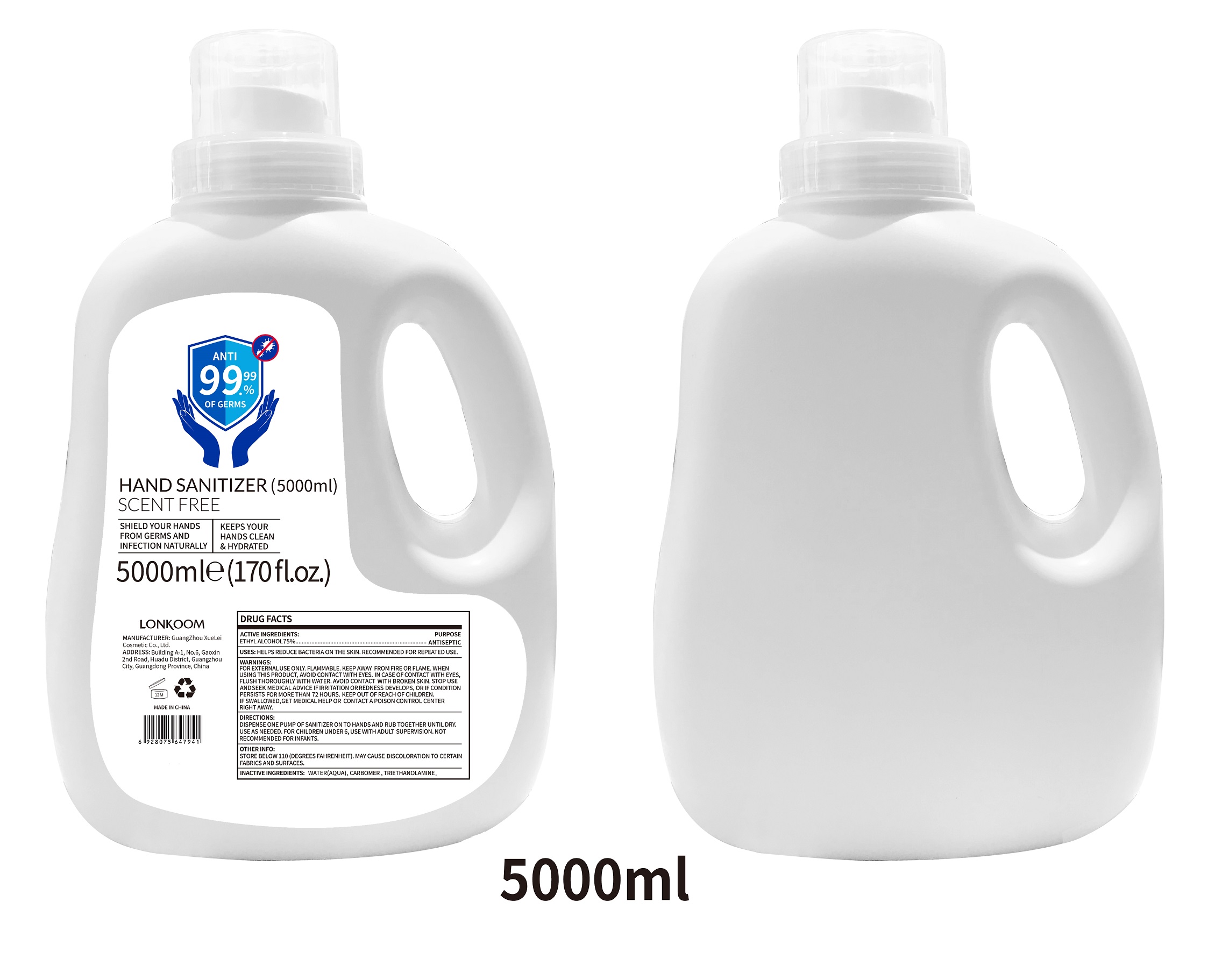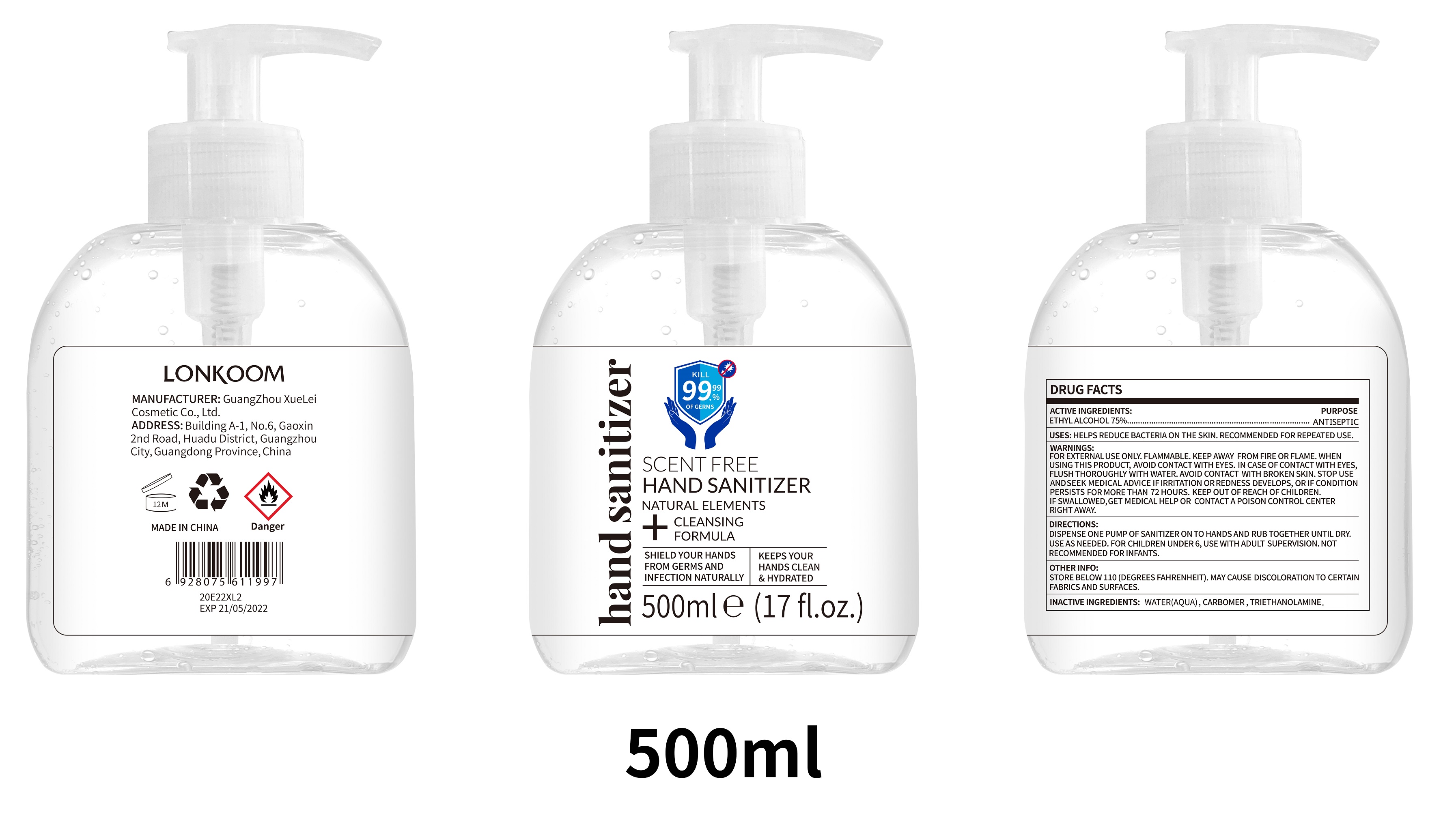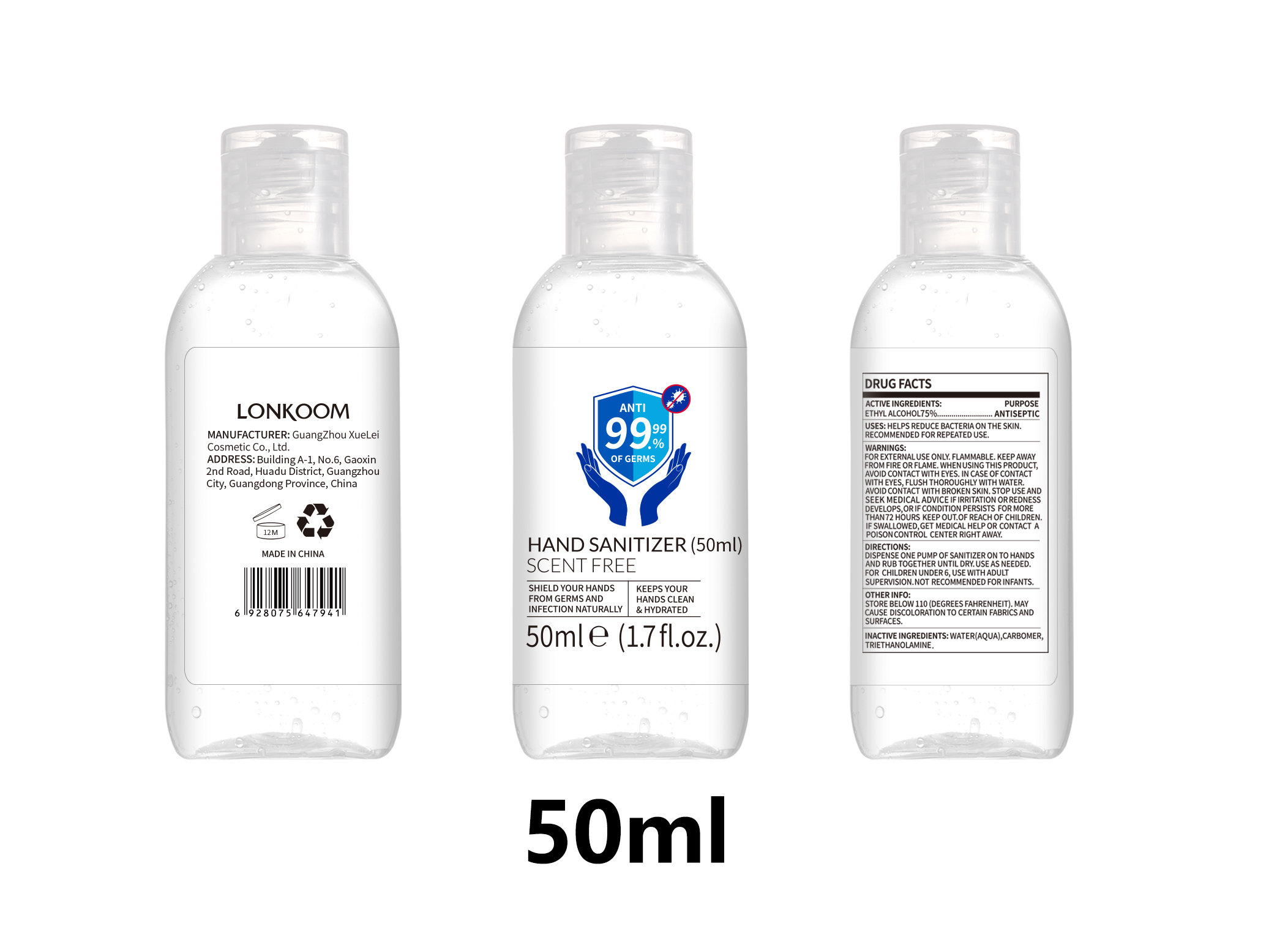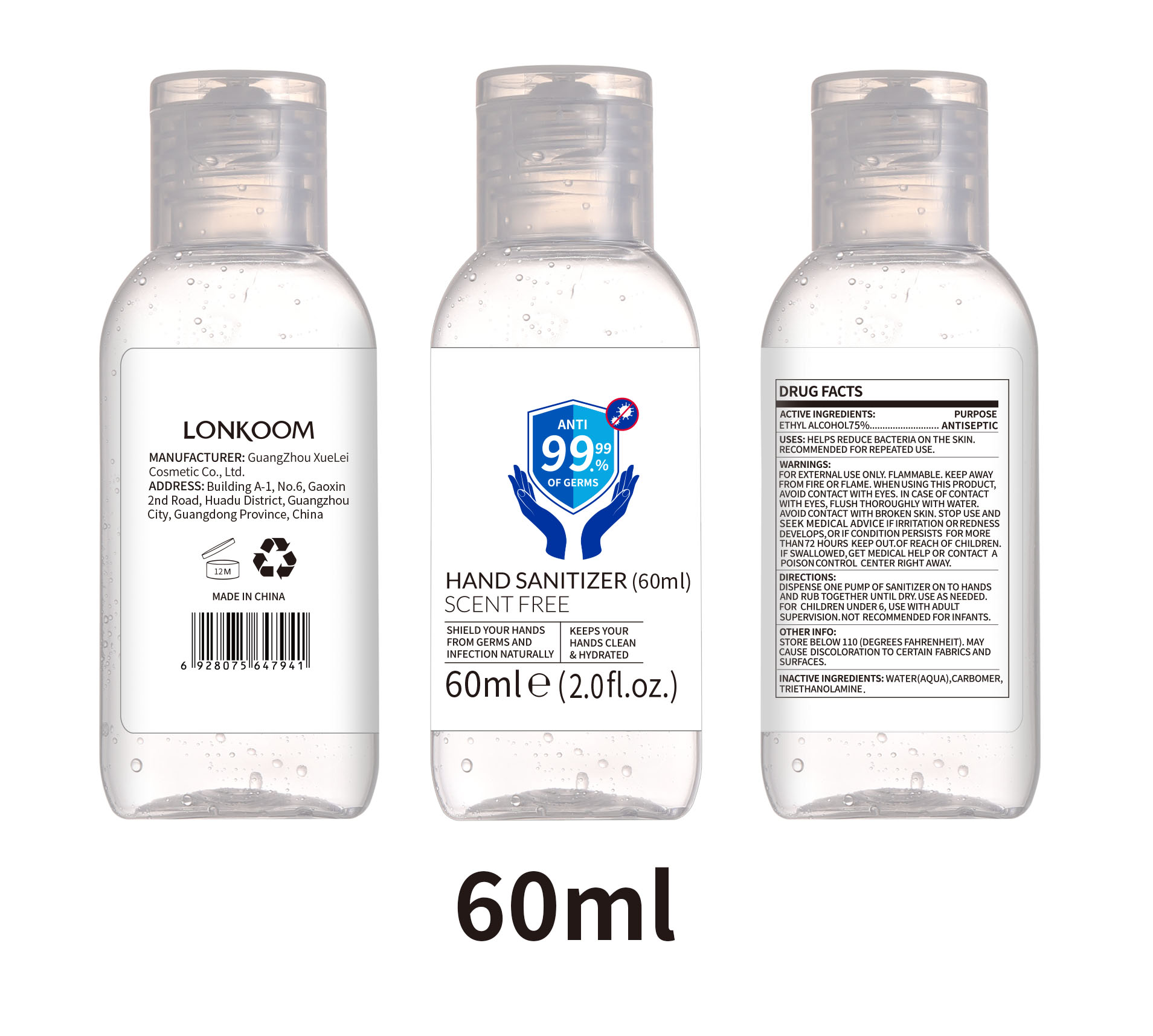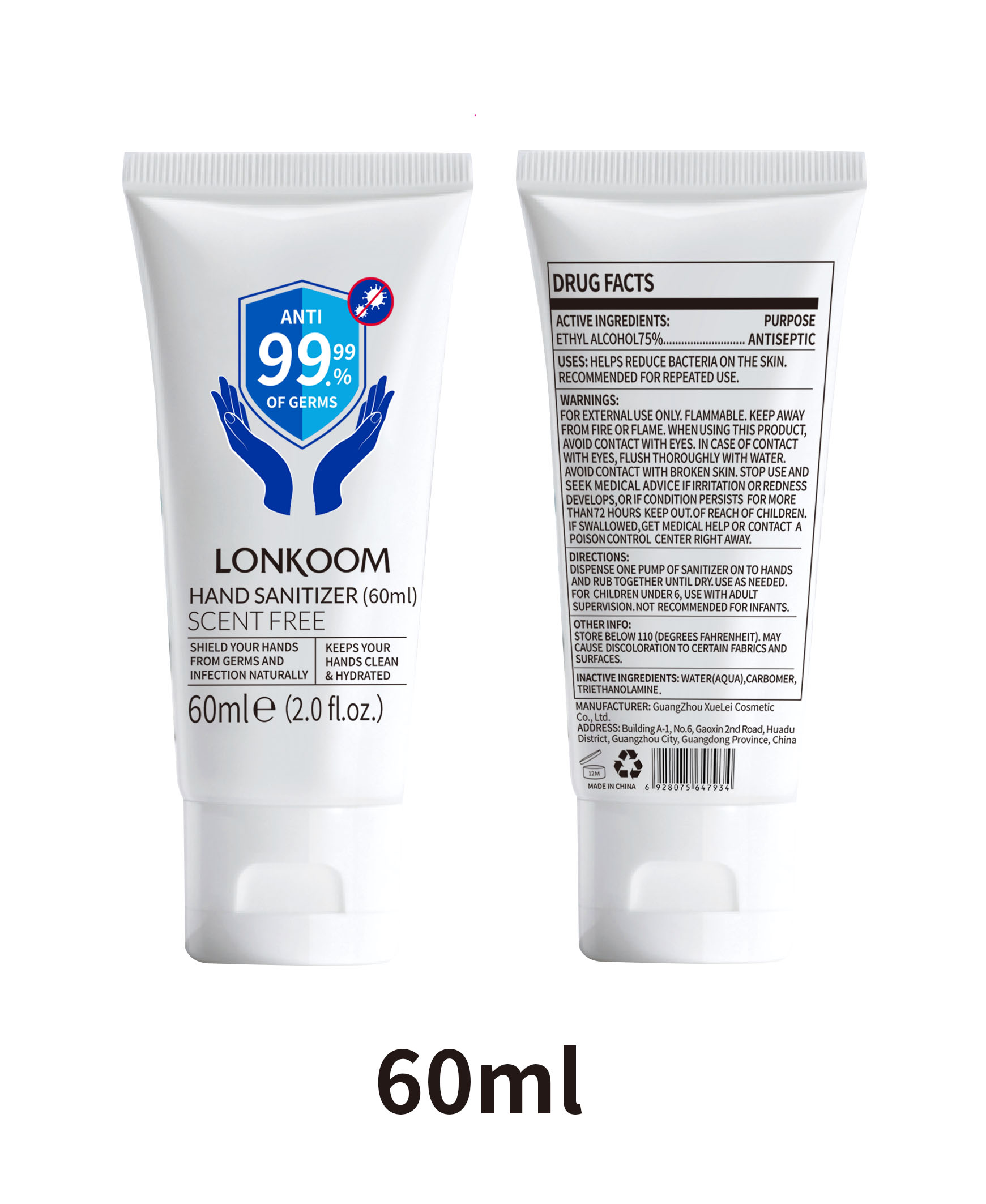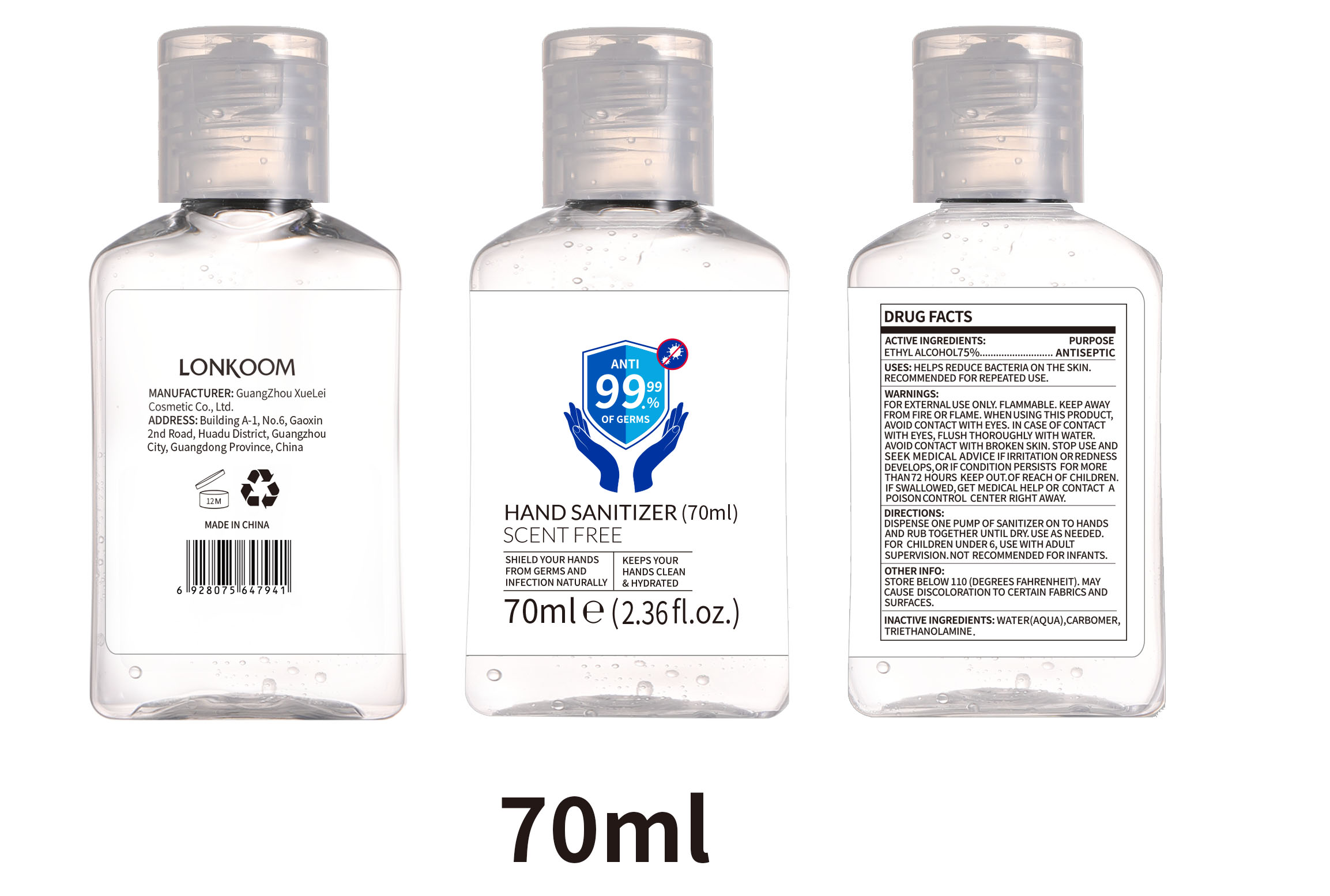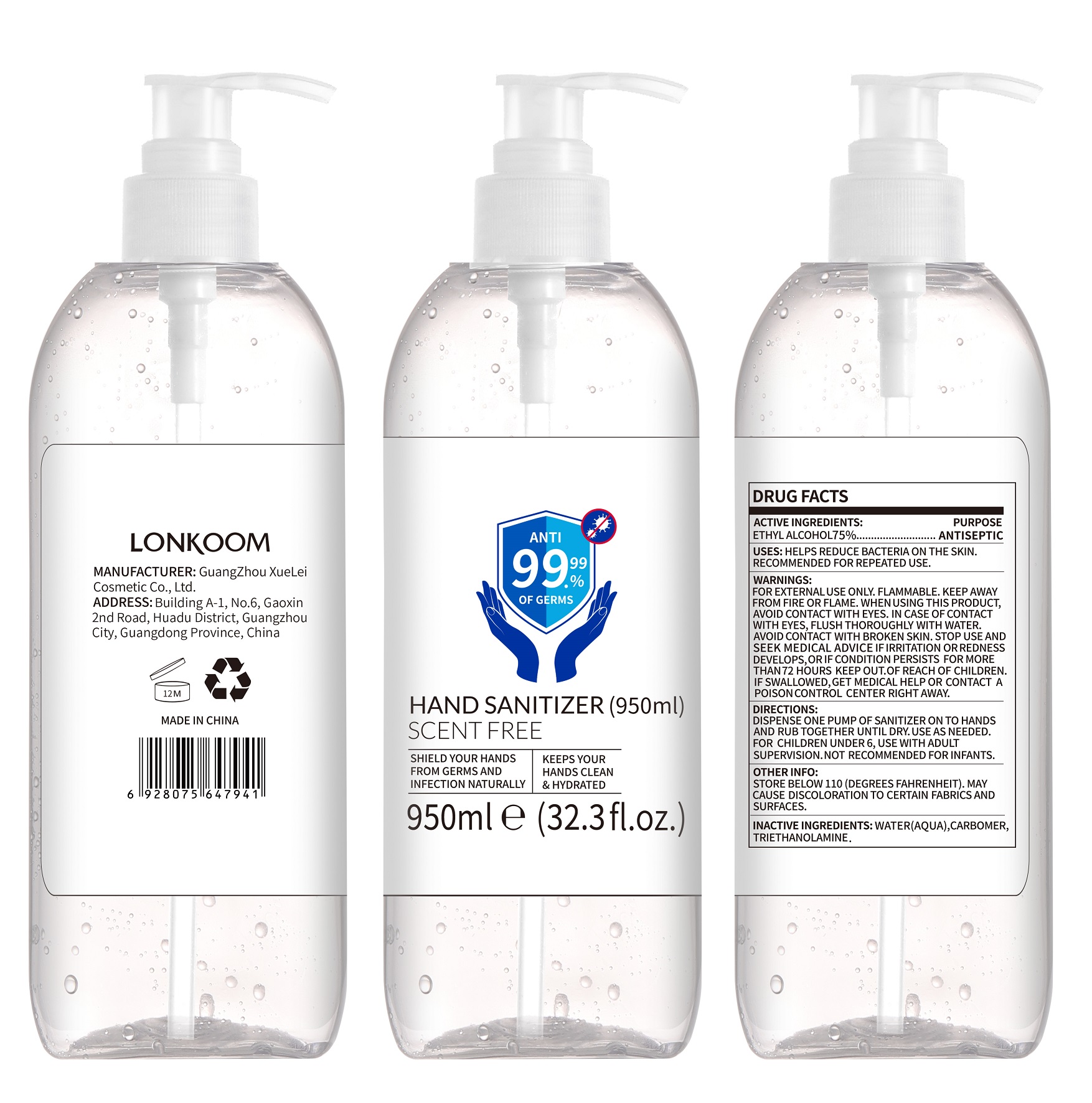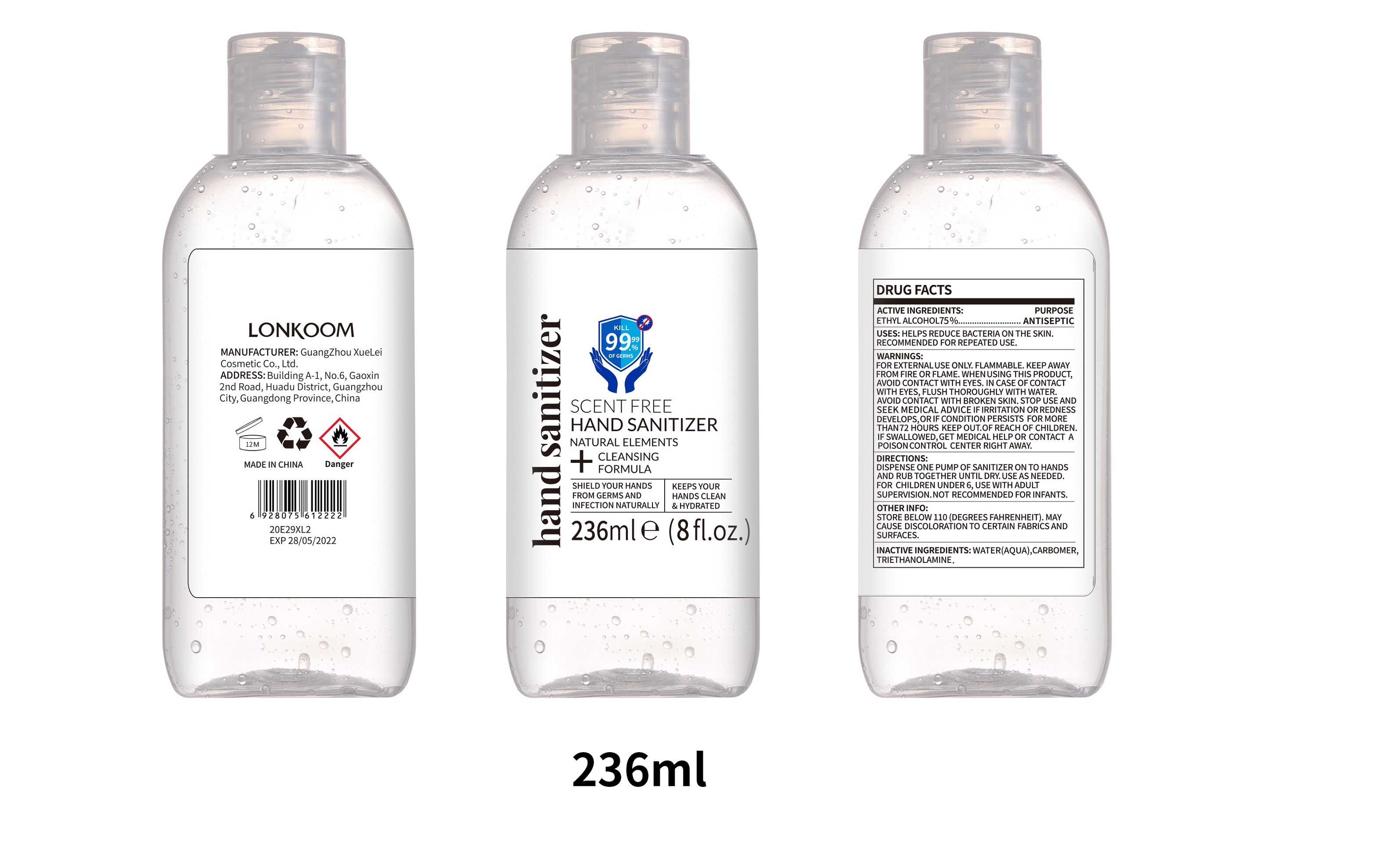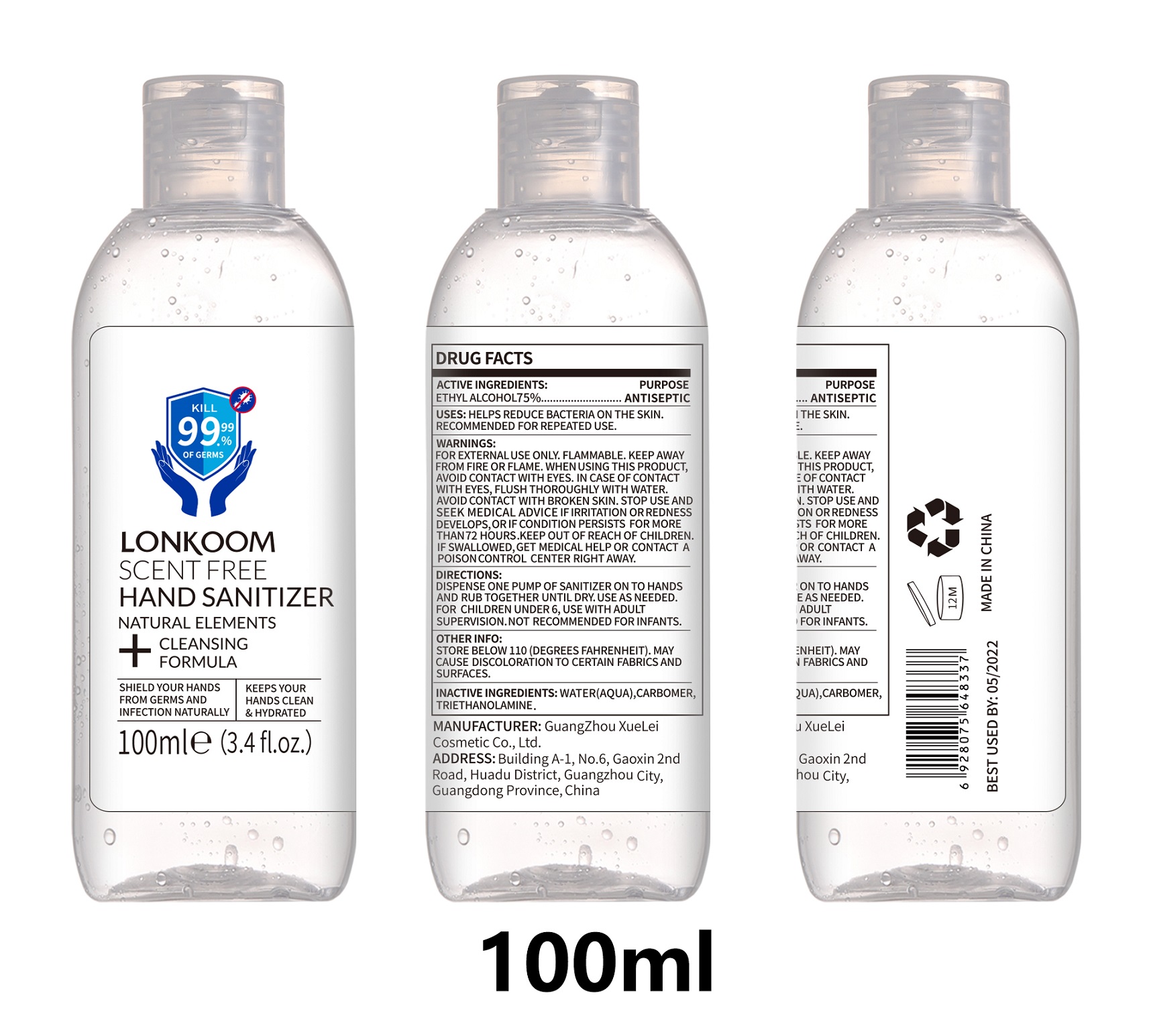 DRUG LABEL: HAND SANITIZER
NDC: 74658-001 | Form: GEL
Manufacturer: GUANGZHOU XUELEI COSMETIC CO.,LTD.
Category: otc | Type: HUMAN OTC DRUG LABEL
Date: 20211104

ACTIVE INGREDIENTS: ALCOHOL 75 mL/100 mL
INACTIVE INGREDIENTS: TROLAMINE 0.22 g/100 mL; CARBOMER HOMOPOLYMER TYPE B (ALLYL PENTAERYTHRITOL CROSSLINKED) 0.4 g/100 mL; WATER 22.19 g/100 mL

HAND SANITIZER

ACTIVE INGREDIENTS:

ETHYL ALCOHOL 75%

PURPOSE

ANTISEPTIC

USES

HELPS REDUCE BACTERIA ON THE SKIN. RECOMMENDED FOR REPEATED USE.

WARNINGS

FOR EXTERNAL USE ONLY. FLAMMABLE. KEEP AWAY FROM FIRE OR FLAME. WHEN USING THIS PRODUCT, AVOID CONTACT WITH EYES. IN CASE OF CONTACT WITH EYES, FLUSH THOROUGHLY WITH WATER. AVOID CONTACT WITH BROKEN SKIN. STOP USE AND SEEK MEDICAL ADVICE IF IRRITATION OR REDNESS DEVELOPS, OR IF CONDITION PERSISTS FOR MORE THAN 72 HOURS. KEEP OUT OF REACH OF CHILDREN. IF SWALLOWED, GET MEDICAL HELP OR CONTACT A POISON CONTROL CENTER RIGHT AWAY.

KEEP OUT OF REACH OF CHILDREN.

DIRECTIONS

DISPENSE ONE PUMP OF SANITIZER ON TO HANDS AND RUB TOGETHER UNTIL DRY. USE AS NEEDED. FOR CHILDREN UNDER 6, USE WITH ADULT SUPERVISION. NOT RECOMMENDED FOR INFANTS.

OTHER INFO

STORE BELOW 110 (DEGREES FAHRENHEIT). MAY CAUSE DISCOLORATION TO CERTAIN FABRICS AND SURFACES.

INACTIVE INGREDIENTS

WATER (AQUA), CARBOMER, TRIETHANOLAMINE.

Package Label

HAND SANITIZER (60ml)

SCENT FREE

SHIELD YOUR HANDS FROM GERMS AND INFECTION NATURALLY

KEEPS YOUR HANDS CLEAN & HYDRATED

60ml e (2.0 fl.oz.)

NDC: 74658-001-01

Package Label

HAND SANITIZER (60ml)

SCENT FREE

SHIELD YOUR HANDS FROM GERMS AND INFECTION NATURALLY

KEEPS YOUR HANDS CLEAN & HYDRATED

60ml e (2.0 fl.oz.)

NDC: 74658-001-02

Package Label

HAND SANITIZER (70ml)

SCENT FREE

SHIELD YOUR HANDS FROM GERMS AND INFECTION NATURALLY

KEEPS YOUR HANDS CLEAN & HYDRATED

70ml e (2.36 fl.oz.)

NDC: 74658-001-03

Package Label

100ml e (3.4 fl.oz.)

NDC: 74658-001-04

Package Label

HAND SANITIZER (120ml)

SCENT FREE

SHIELD YOUR HANDS FROM GERMS AND INFECTION NATURALLY

KEEPS YOUR HANDS CLEAN & HYDRATED

120ml e (4.0 fl.oz.)

NDC: 74658-001-05

Package Label

236ml e (8 fl.oz.)

NDC: 74658-001-06

Package Label

HAND SANITIZER (250ml)

SCENT FREE

SHIELD YOUR HANDS FROM GERMS AND INFECTION NATURALLY

KEEPS YOUR HANDS CLEAN & HYDRATED

250ml e (8.5 fl.oz.)

NDC: 74658-001-07

Package Label

HAND SANITIZER (260ml)

SCENT FREE

SHIELD YOUR HANDS FROM GERMS AND INFECTION NATURALLY

KEEPS YOUR HANDS CLEAN & HYDRATED

260ml e (8.8 fl.oz.)

NDC: 74658-001-08

Package Label

HAND SANITIZER (290ml)

SCENT FREE

SHIELD YOUR HANDS FROM GERMS AND INFECTION NATURALLY

KEEPS YOUR HANDS CLEAN & HYDRATED

290ml e (9.8 fl.oz.)

NDC: 74658-001-09

Package Label

HAND SANITIZER (300ml)

SCENT FREE

SHIELD YOUR HANDS FROM GERMS AND INFECTION NATURALLY

KEEPS YOUR HANDS CLEAN & HYDRATED

300ml e (10.2 fl.oz.)

NDC: 74658-001-10

Package Label

500ml e (17 fl.oz.)

NDC: 74658-001-11

Package Label

HAND SANITIZER (950ml)

SCENT FREE

SHIELD YOUR HANDS FROM GERMS AND INFECTION NATURALLY

KEEPS YOUR HANDS CLEAN & HYDRATED

950ml e (32.3 fl.oz.)

NDC: 74658-001-12

Package Label

HAND SANITIZER (1000ml)

SCENT FREE

SHIELD YOUR HANDS FROM GERMS AND INFECTION NATURALLY

KEEPS YOUR HANDS CLEAN & HYDRATED

1000ml e (34 fl.oz.)

NDC: 74658-001-13

Package Label

HAND SANITIZER (2000ml)

SCENT FREE

SHIELD YOUR HANDS FROM GERMS AND INFECTION NATURALLY

KEEPS YOUR HANDS CLEAN & HYDRATED

2000ml e (68 fl.oz.)

NDC: 74658-001-14

Package Label

HAND SANITIZER (30ml)

SCENT FREE

SHIELD YOUR HANDS FROM GERMS AND INFECTION NATURALLY

KEEPS YOUR HANDS CLEAN & HYDRATED

30ml e (1.0 fl.oz.)

NDC: 74658-001-15

Package Label

HAND SANITIZER (40ml)

SCENT FREE

SHIELD YOUR HANDS FROM GERMS AND INFECTION NATURALLY

KEEPS YOUR HANDS CLEAN & HYDRATED

40ml e (1.35 fl.oz.)

NDC: 74658-001-16

Package Label

HAND SANITIZER (50ml)

SCENT FREE

SHIELD YOUR HANDS FROM GERMS AND INFECTION NATURALLY

KEEPS YOUR HANDS CLEAN & HYDRATED

50ml e (1.7 fl.oz.)

NDC: 74658-001-17

Package Label

HAND SANITIZER (3785ml)

SCENT FREE

SHIELD YOUR HANDS FROM GERMS AND INFECTION NATURALLY

KEEPS YOUR HANDS CLEAN & HYDRATED

3785ml e (128.68 fl.oz.)

NDC: 74658-001-18

Package Label

HAND SANITIZER (5000ml)

SCENT FREE

SHIELD YOUR HANDS FROM GERMS AND INFECTION NATURALLY

KEEPS YOUR HANDS CLEAN & HYDRATED

5000ml e (170 fl.oz.)

NDC: 74658-001-19

Package Label

HAND SANITIZER (236ml)

SCENT FREE

SHIELD YOUR HANDS FROM GERMS AND INFECTION NATURALLY

KEEPS YOUR HANDS CLEAN & HYDRATED

236ml e (8 fl.oz.)